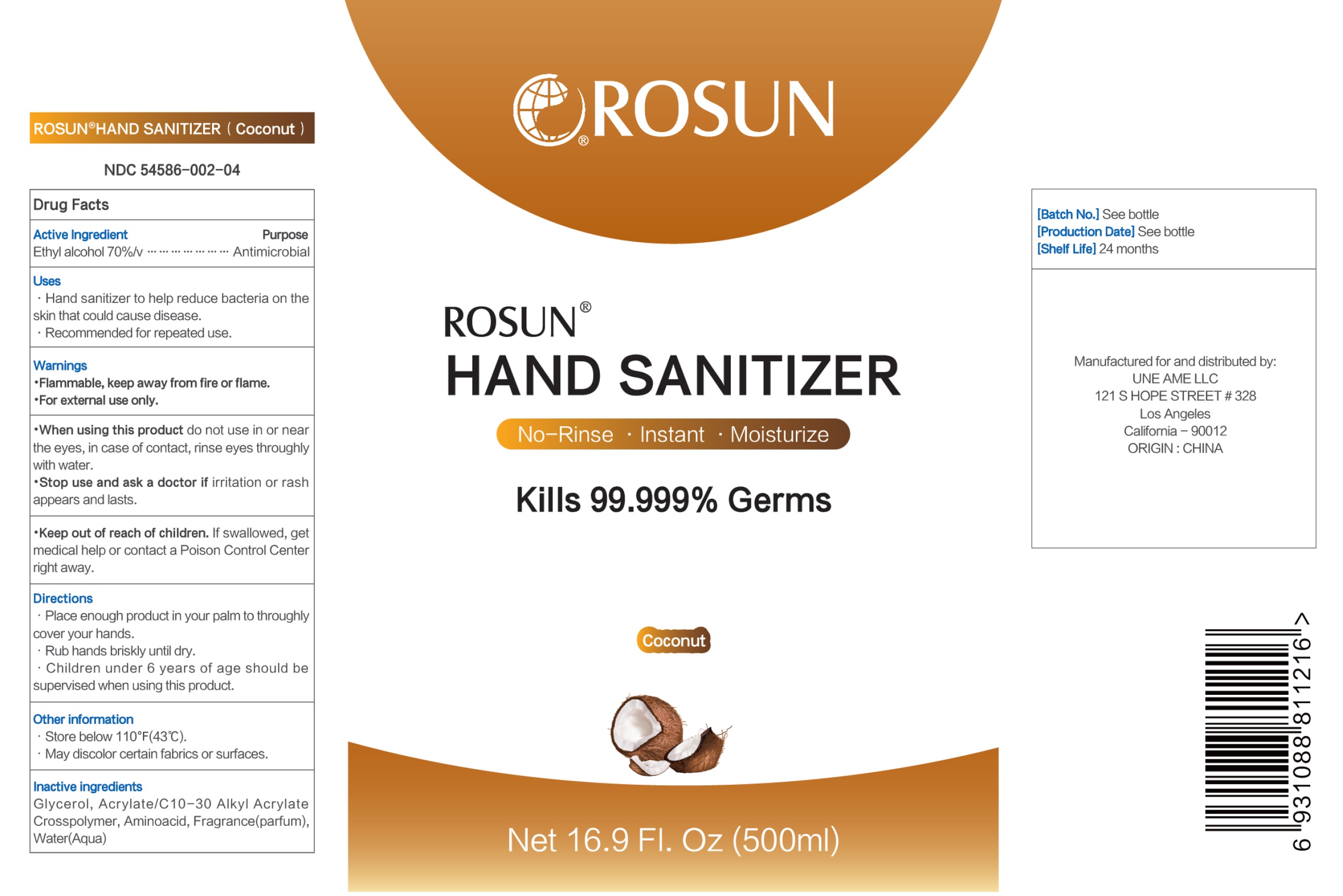 DRUG LABEL: Rosun Hand Sanitizer Coconut
NDC: 81432-003 | Form: GEL
Manufacturer: Une Ame LLC
Category: otc | Type: HUMAN OTC DRUG LABEL
Date: 20210223

ACTIVE INGREDIENTS: ALCOHOL 70 mL/100 mL
INACTIVE INGREDIENTS: GLYCERIN; CARBOMER INTERPOLYMER TYPE A (ALLYL SUCROSE CROSSLINKED); AMINO ACIDS, SOURCE UNSPECIFIED; WATER

Rosun Hand Sanitizer Coconut

Active Ingredient

Ethyl Alcohol 70%/v

Purpose

Antimicrobial

Uses

- Hand sanitizer to help reduce bacteria on the skin that could cause disease.
- Recommended for repeated use.

Warnings

- Flammable, keep away from fire or flame.
- For external use only.

When using this product

- do not use in or near the eyes, in case of contact; rinse eyes thoroughly with water.

Stop use and ask a doctor if

- irritation or rash appears and lasts.

Keep out of reach of children.

- If swallowed, get medical help or contact a Poison control Center right away.

Directions

- Place enough product in your palm to throughly cover your hands.
- Rub hands briskly until dry.
- Children under 6 years of age should be supervised when using this product.

Other information

- Store below 110°F (43°C).
- May discolor certain fabrics or surfaces.

Inactive ingredients

Glycerol, Acrylate/C10-30 Alkyl Acrylate Crosspolymer, Aminoacid, Fragrance(parfum), Water(Aqua)